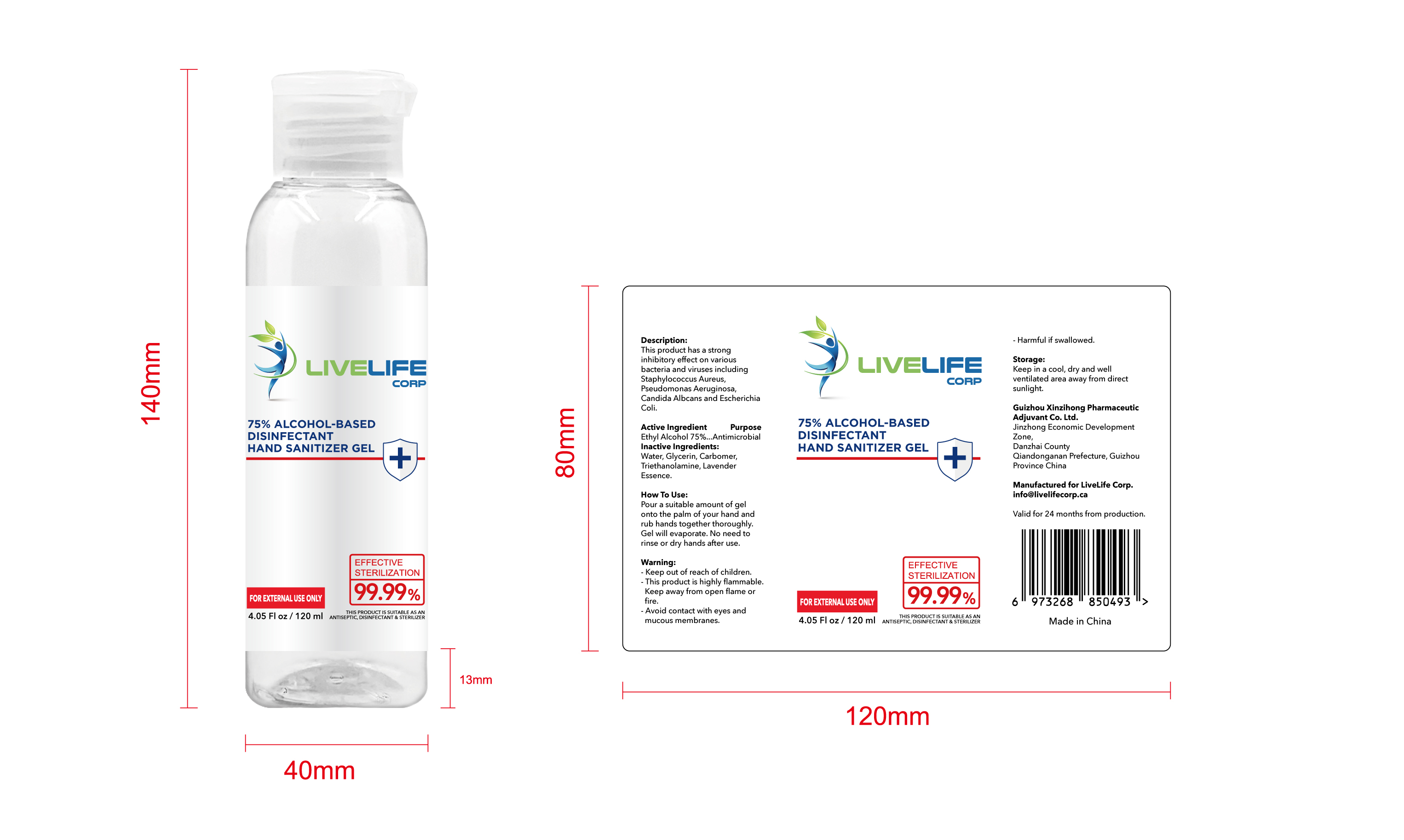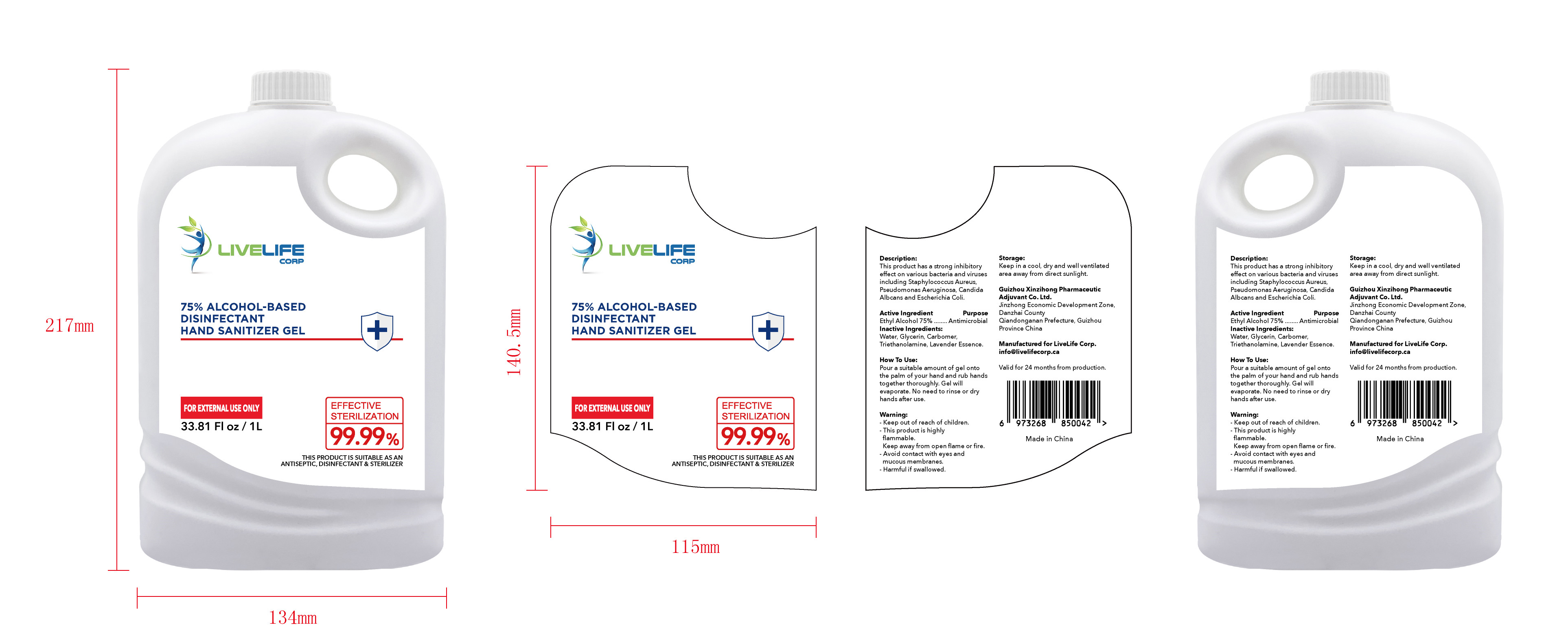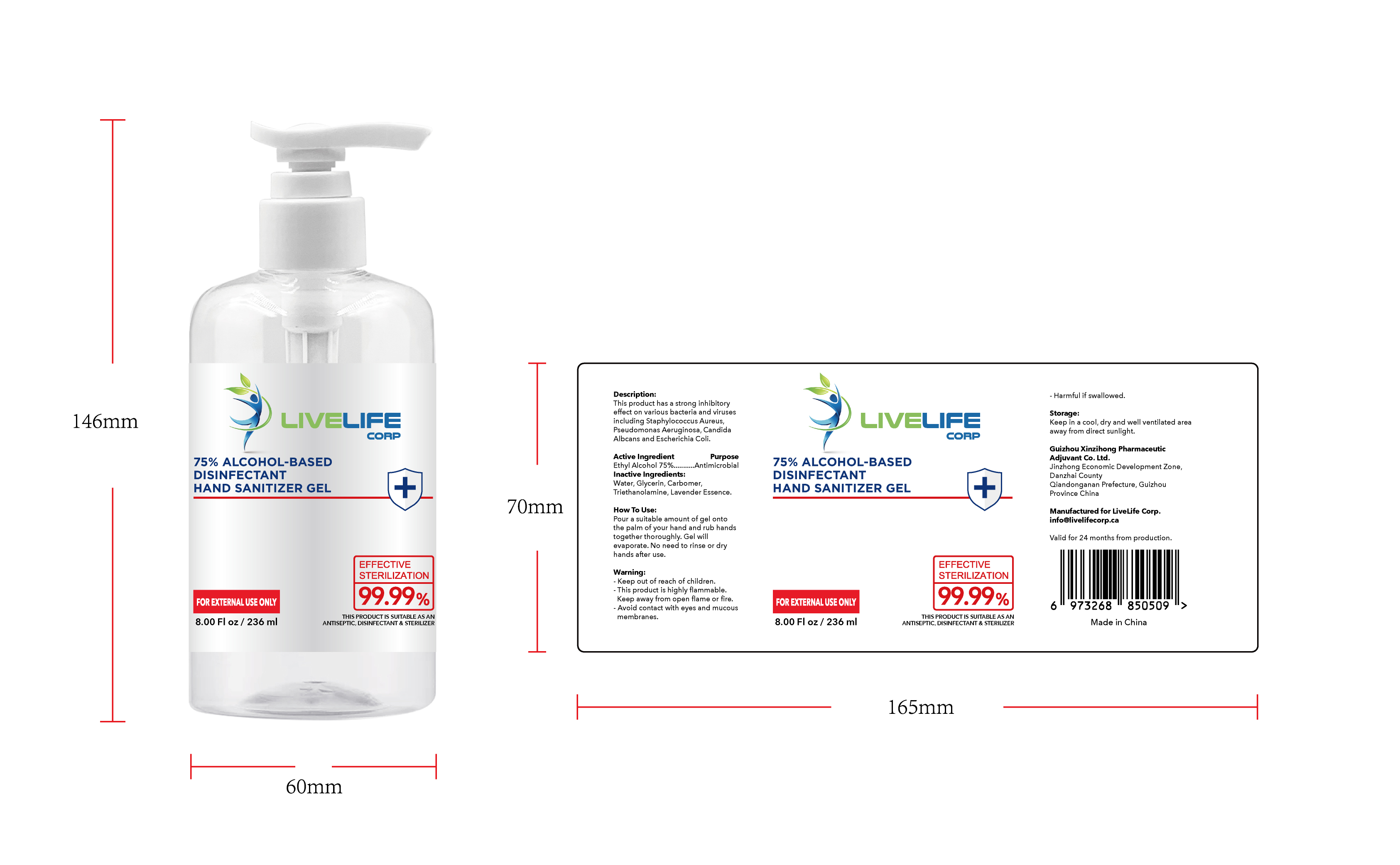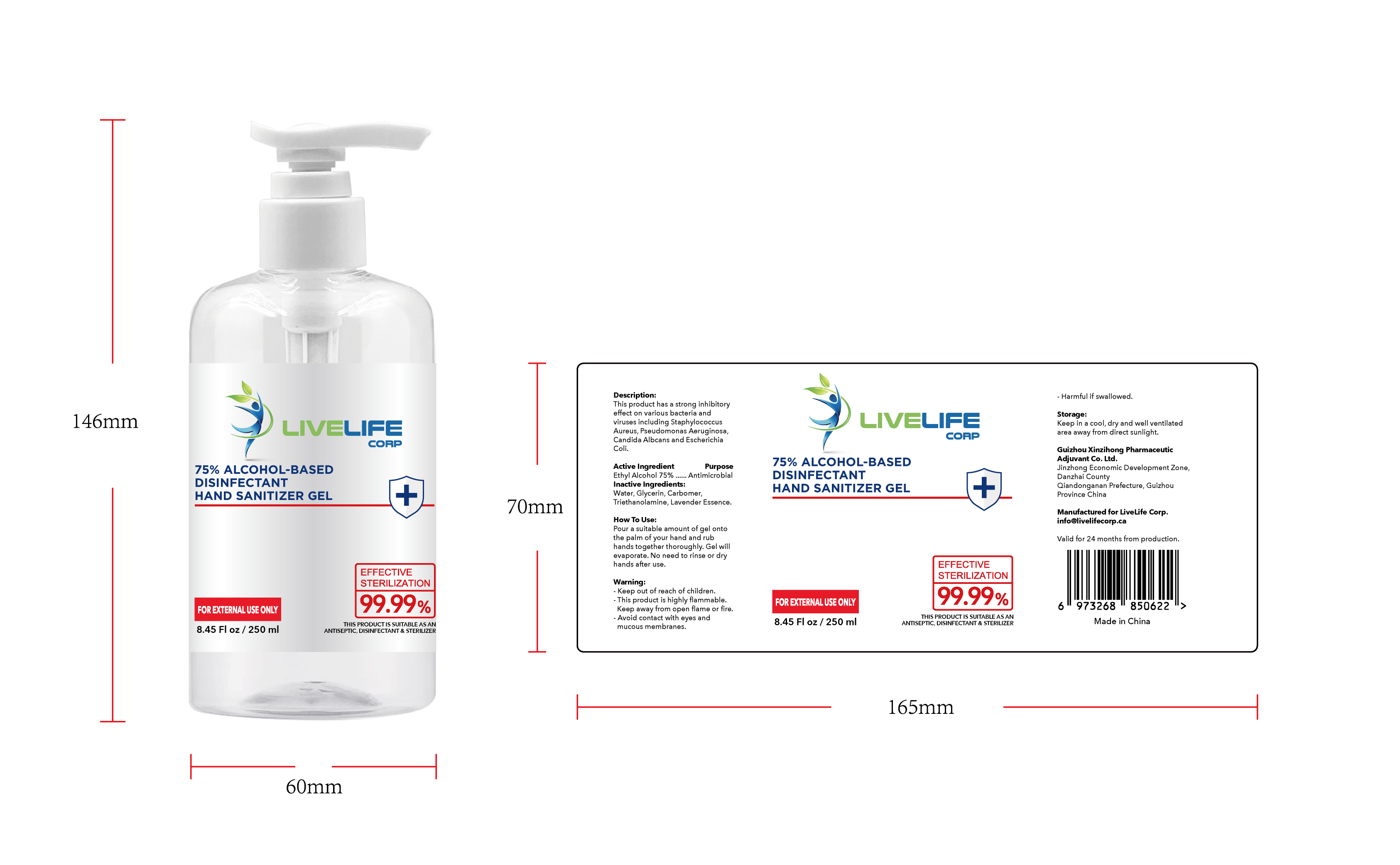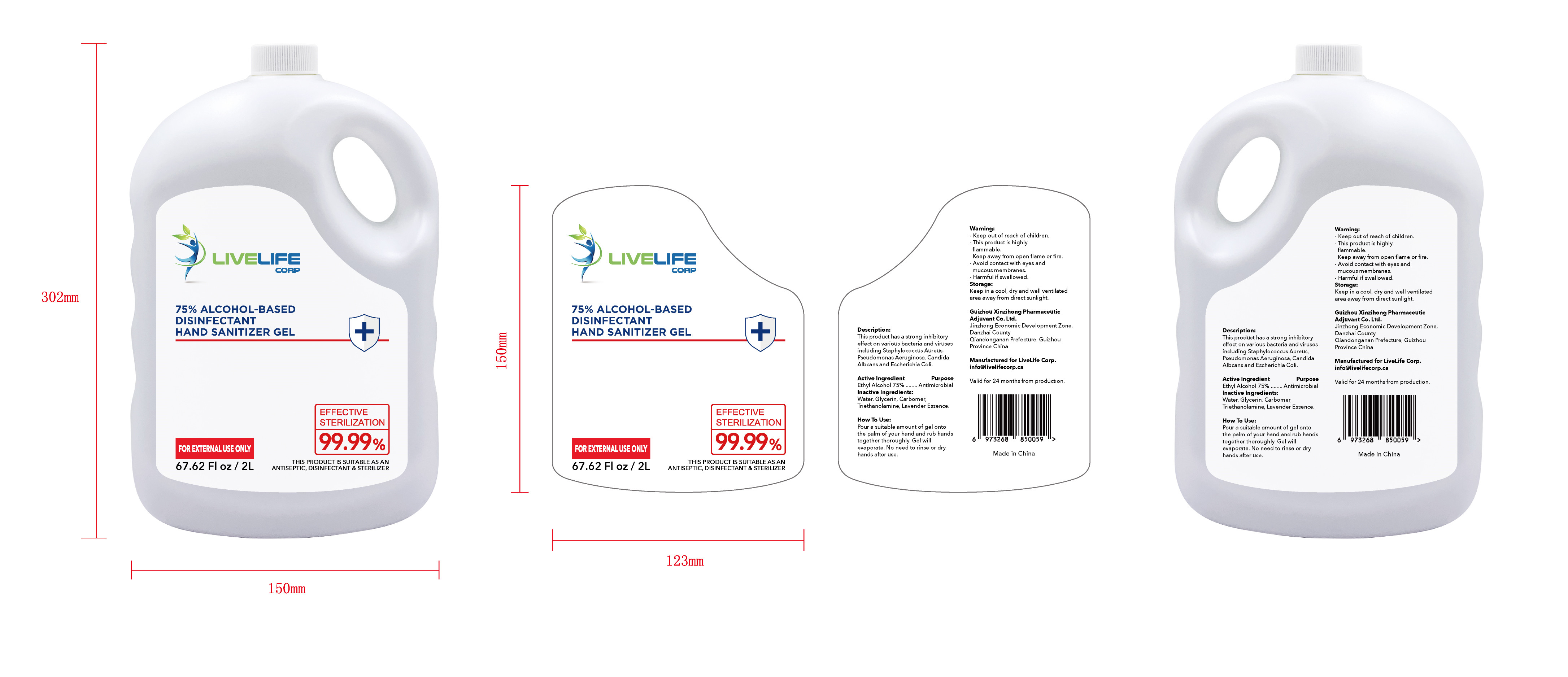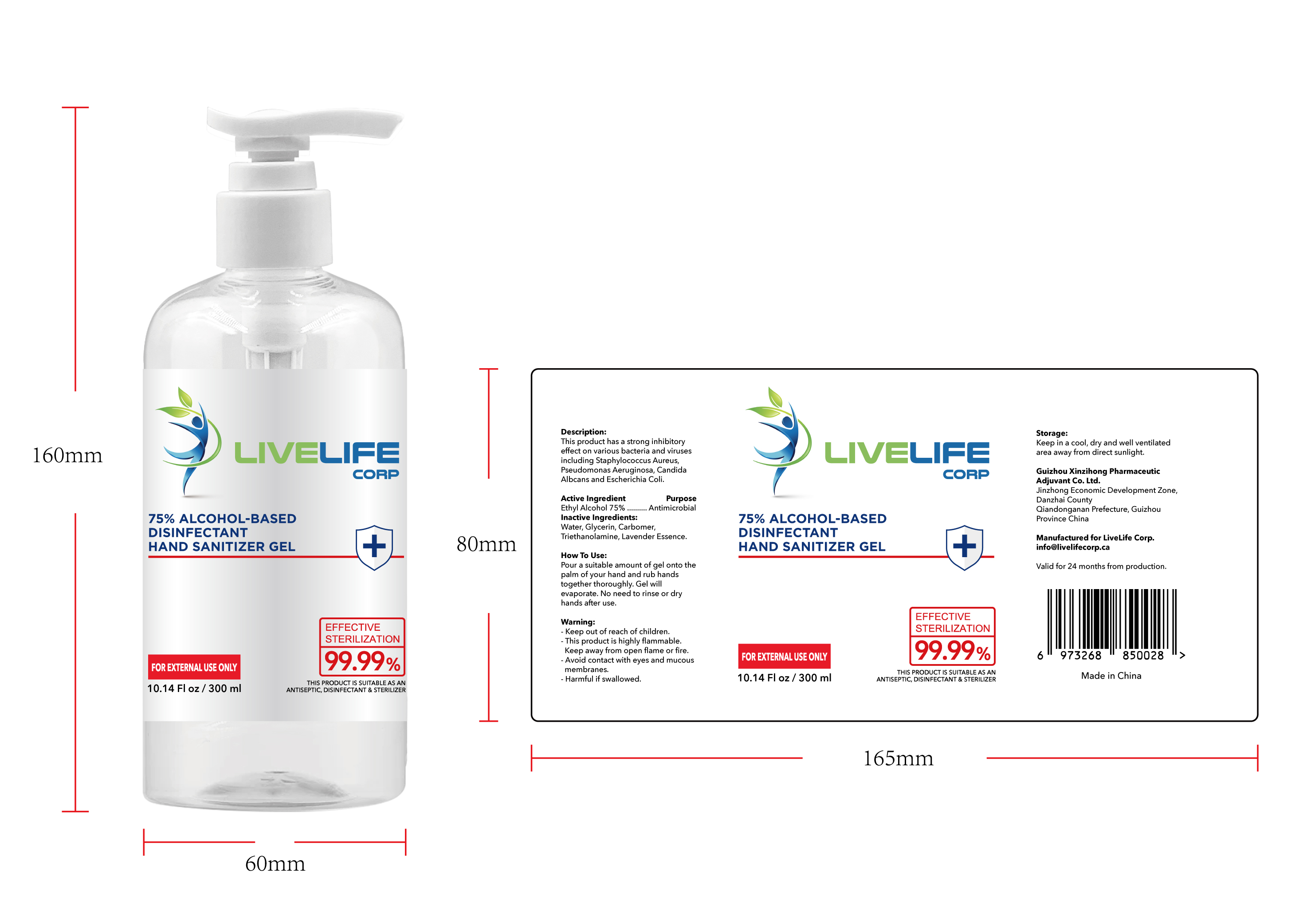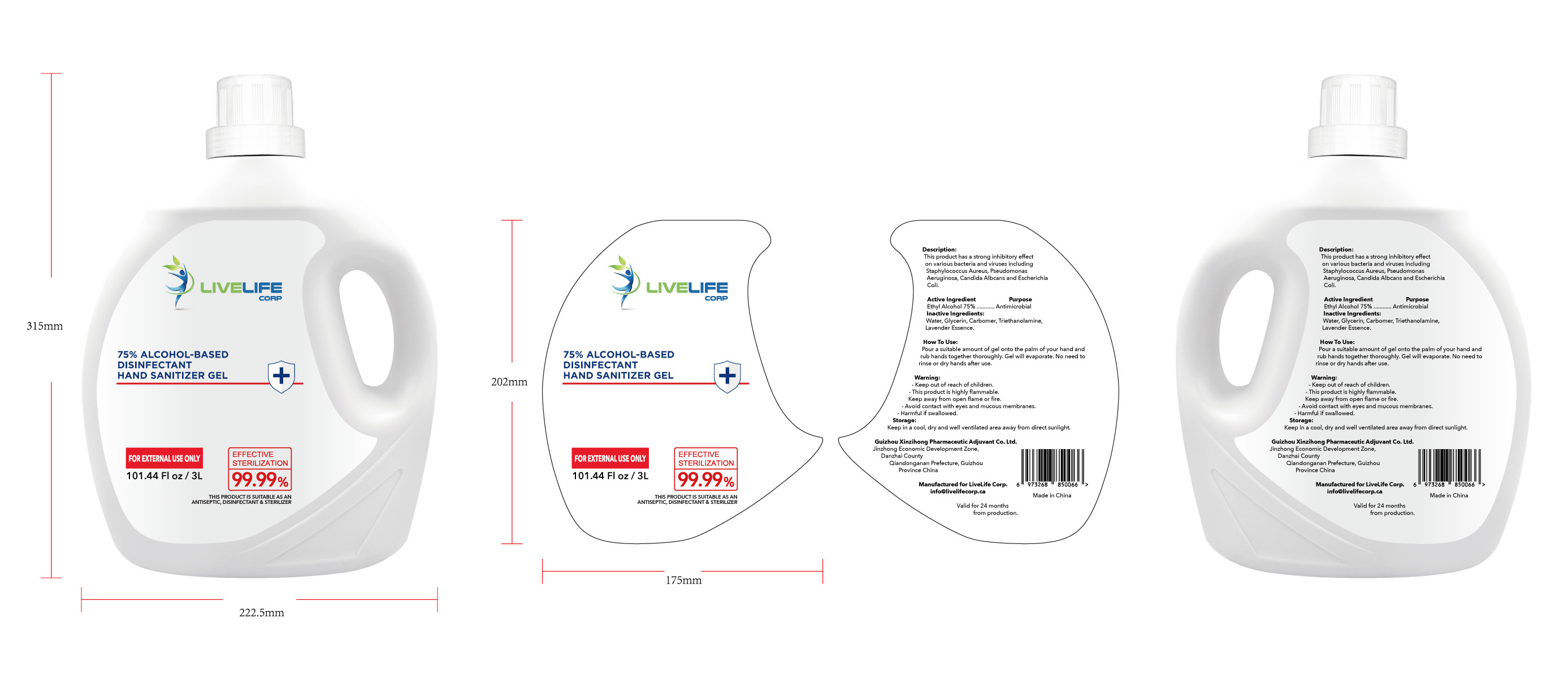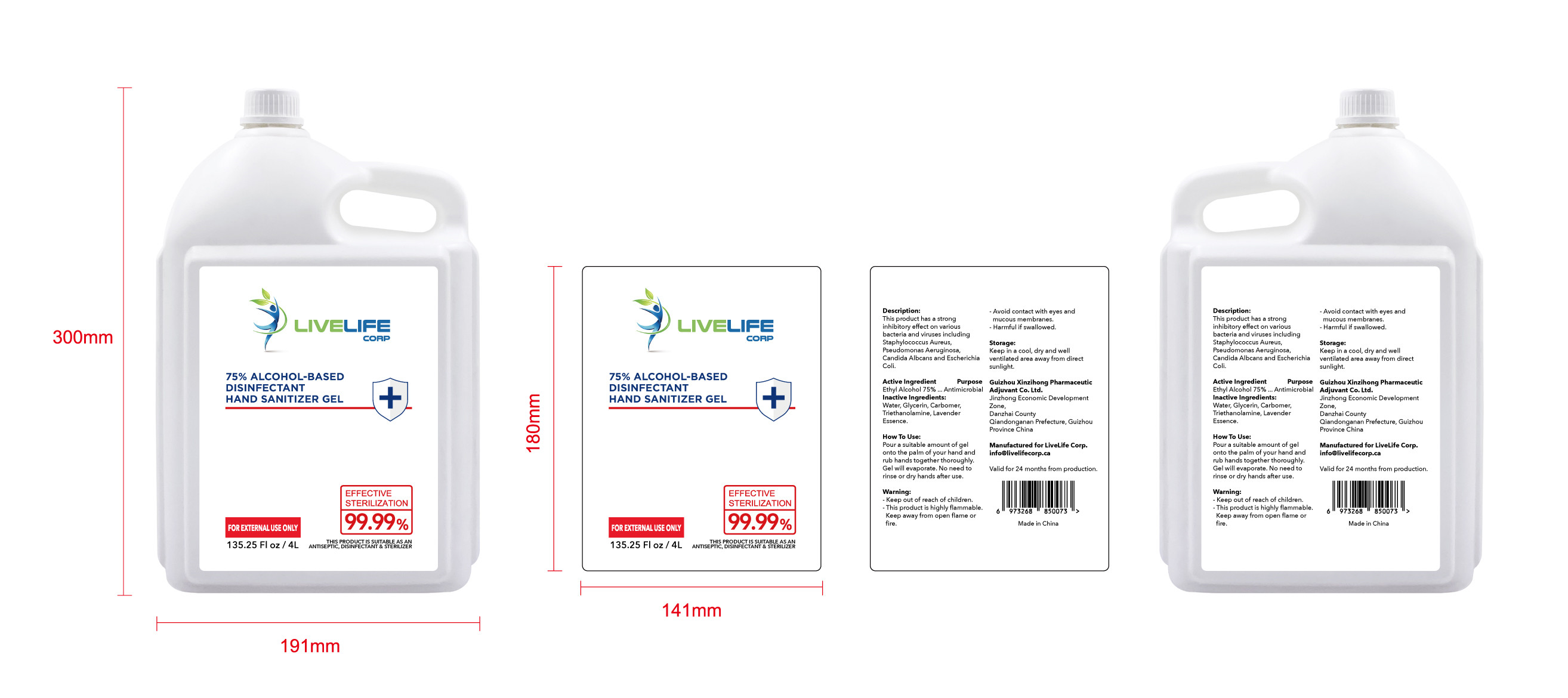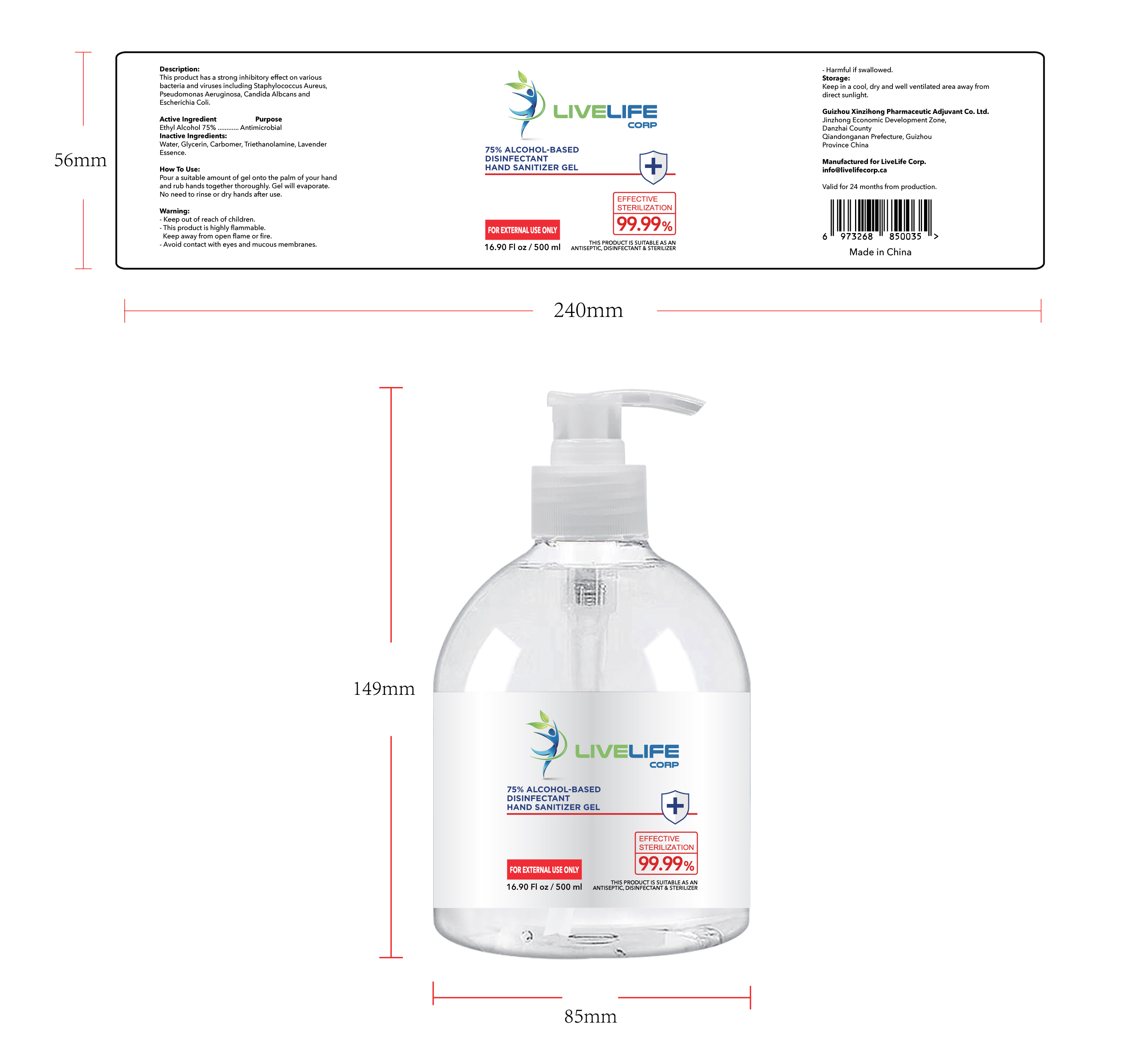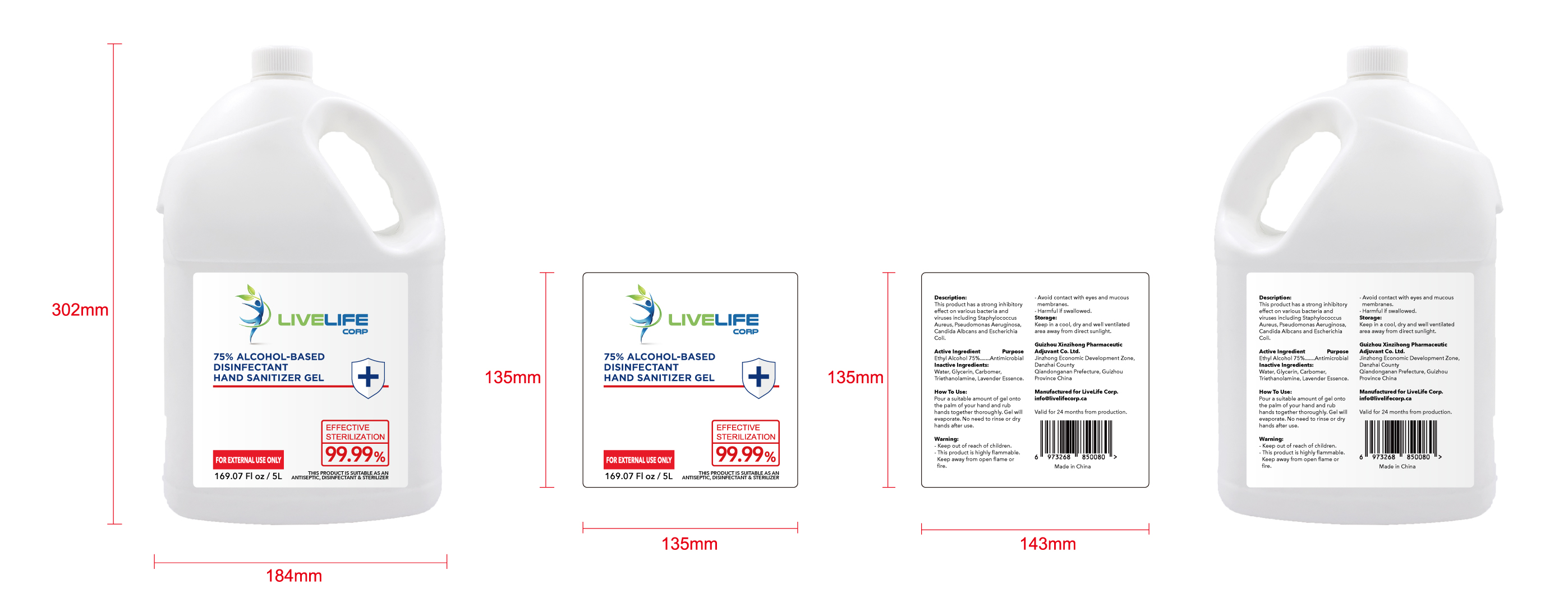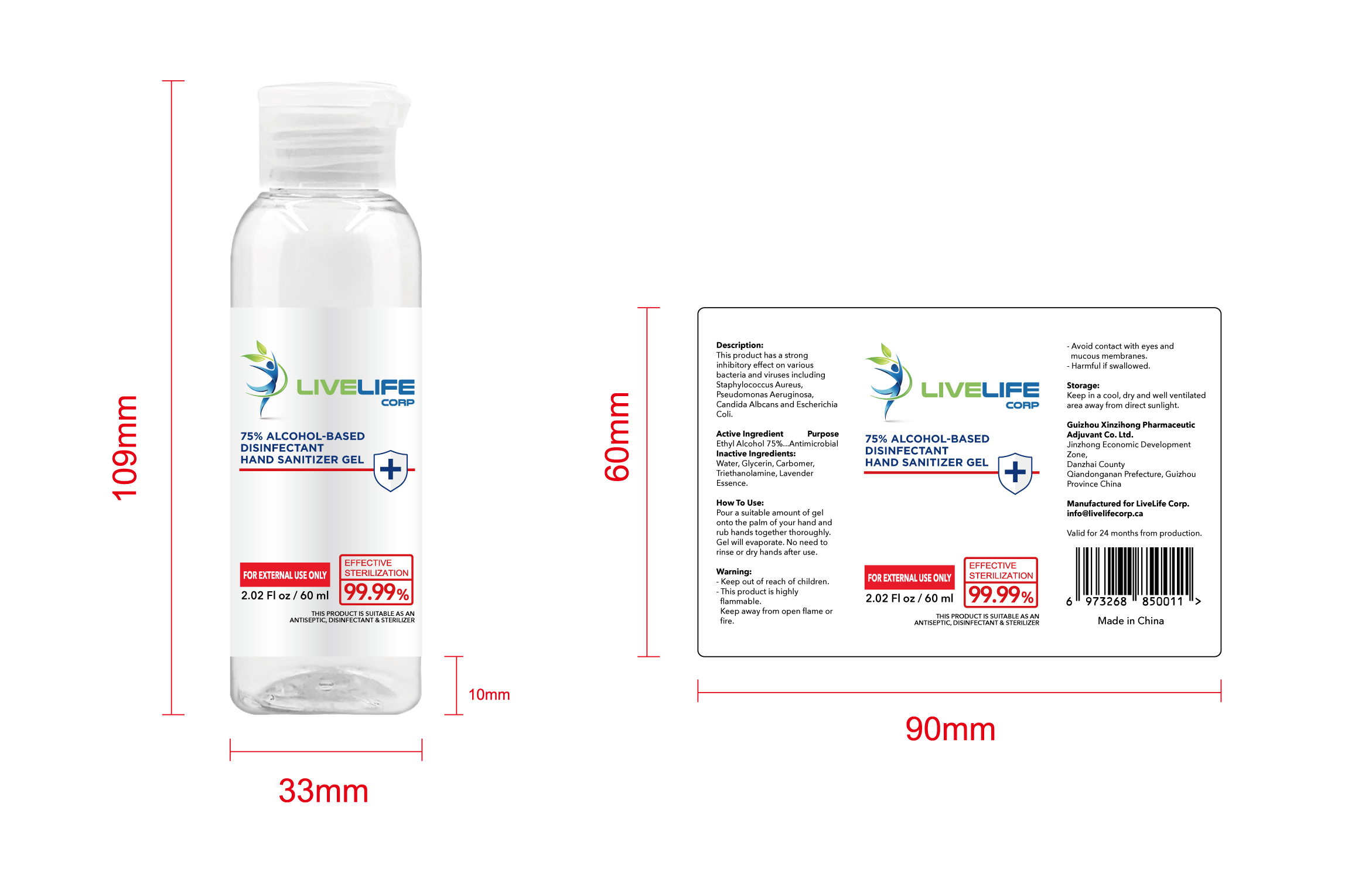 DRUG LABEL: ALCOHOL-BASED DISINFECTANT HAND SANITIZER
NDC: 79606-001 | Form: GEL
Manufacturer: Foshan Lang-Yeon Trade Limited Company
Category: otc | Type: HUMAN OTC DRUG LABEL
Date: 20200710

ACTIVE INGREDIENTS: ALCOHOL 75 mL/100 mL
INACTIVE INGREDIENTS: GLYCERIN; TROLAMINE; WATER; CARBOMER COPOLYMER TYPE A (ALLYL PENTAERYTHRITOL CROSSLINKED)

Active Ingredient(s)

Ethyl Alcohol 75% v/v. Purpose: Antimicrobial

Purpose

Purpose: Antimicrobial , Hand Sanitizer

Use

Pour a suitable amount of gel onto the palm of your hand and rub hands together thoroughly. Gel will evaporate. No need to rinse or dry hands after use

Warnings

Keep out of reach of children This product is highly flammable Keep away from open flame or fire Avoid contact with eyes and mucous membranes Harmful if swallowed

Do not use

/

WHEN USING

/

STOP USE

/

Directions

This product has a strong inhibitoryffect on various bacteria and virusesincluding Staphylococcus Aureus,

Pseudomonas Aeruginosa, CandidaAlbcans and Escherichia Coli

Other information

Keep in a cool, dry and well ventilated area away from direct sunlight

Inactive ingredients

Water, Glycerin, Carbomer,Triethanolamine, Lavender Essence